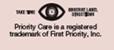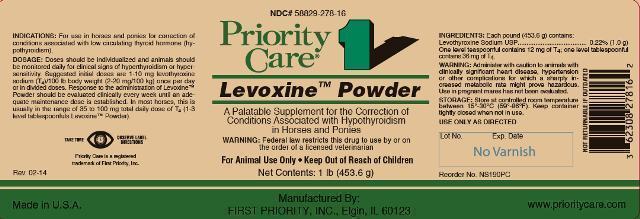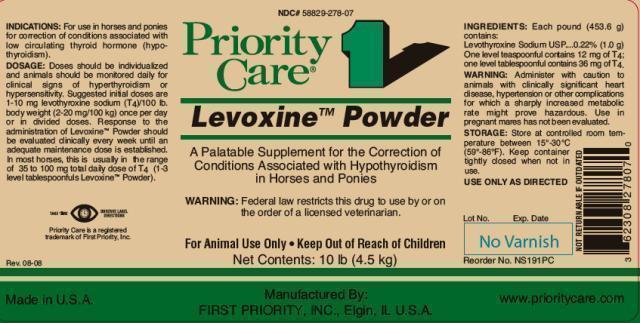 DRUG LABEL: Levoxine
NDC: 58829-278 | Form: POWDER
Manufacturer: First Priority Incorporated
Category: animal | Type: PRESCRIPTION ANIMAL DRUG LABEL
Date: 20180907

ACTIVE INGREDIENTS: LEVOTHYROXINE SODIUM 1000 mg/453.6 g

Levoxine™ Powder

INFORMATION FOR OWNERS/CAREGIVERS

A Palatable Supplement for the Correction of Conditions Associated with Hypothyroidism in Horses and Ponies.

WARNINGS AND PRECAUTIONS

WARNING: Federal law restricts this drug to use by or on the order of a licensed veterinarian.

For Animal Use Only • Keep Out of Reach of Children

INDICATIONS:

For use in horses and ponies for correction of conditions associated with low circulating thyroid hormone (hypothyrodism).

DOSAGE:

Doses should be individualized and animals should be monitored daily for clincial signs of hyperthyroidism or hypersensitivity. Suggested initial doses are 1-10 mg levothyroxine sodium (T4)/100 lb body weight (2-20 mg/100 kg) once per day or in divided doses. Response to the administration of Levoxine™ Powder should be evaluated clinically every week until an adequate maintenance dose is established. In most horses, this is usually in the range of 35 to 100 mg total daily dose of T4 (1-3 level tablespoonfuls Levoxine™ Powder).

INGREDIENTS:

Each pound (453.6 g) contains:

Levothyroxine Sodium USP ........................................ 0.22% (1.0 g)

One level teaspoonful contains 12 mg of T4: one level tablespoonful contains 36 mg of T4.

WARNINGS

WARNING: Administer with caution to animals with clincially significant heart disease, hypertension or other complications for which a sharply increased metabolic rate might prove hazardous. Use in pregnant mares has not been evaluated.

STORAGE AND HANDLING

STORAGE: Store at controlled room temperature between 15° - 30°C (59° - 86°F). Keep container tightly closed when not in use.

USE ONLY AS DIRECTED

HOW SUPPLIED

Net Contents:

1 lb (453.6 grams), Reorder No. NS190PC

10 lb (4.5 kg), Reorder No. NS191PC

INFORMATION FOR OWNERS/CAREGIVERS

USE ONLY AS DIRECTED

Made in U.S.A.

Manufactured By:

First Priority, Inc., Elgin, IL 60123

www.prioritycare.com

NOT RETURNABLE IF OUTDATED